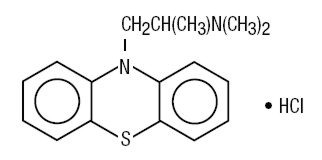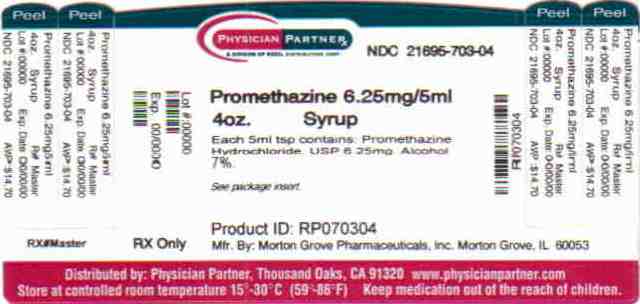 DRUG LABEL: Promethazine Hydrochloride
NDC: 21695-703 | Form: SYRUP
Manufacturer: Rebel Distributors Corp
Category: prescription | Type: HUMAN PRESCRIPTION DRUG LABEL
Date: 20110104

ACTIVE INGREDIENTS: Promethazine Hydrochloride 6.25 mg/5 mL
INACTIVE INGREDIENTS: ascorbic acid; ANHYDROUS CITRIC ACID; D&C YELLOW NO. 10; edetate disodium; FD&C BLUE NO. 1; FD&C RED NO. 40; glycerin; SUCROSE; METHYLPARABEN; water; SACCHARIN SODIUM; sodium benzoate; TRISODIUM CITRATE DIHYDRATE; sodium propionate

PROMETHAZINE HYDROCHLORIDE SYRUP, USP 6.25 mg/5 mL

Rx only

DESCRIPTION

Each 5 mL (teaspoonful) contains:

Promethazine Hydrochloride, USP . . . . . . . . . . . . . . . . . . . . . . . . . . . . . . . 6.25 mg

(In a flavored syrup base with a pH between 4.7 and 5.2)

Alcohol . . . . . . . . . . . . . . . . . . . . . . . . . . . . . . . . . . . . . . . . . . . . . . . . . . . . . . 7.0%

In addition, the following inactive ingredients are present: artificial banana flavor, artificial fruit flavor, artificial strawberry flavor, ascorbic acid, USP, citric acid anhydrous, USP, D&C Yellow No. 10, edetate disodium, USP, FD&C Blue No. 1, FD&C Red No. 40, glycerin, USP, liquid sugar, methylparaben, NF, purified water, USP, saccharin sodium, USP, sodium benzoate, NF, sodium citrate dihydrate, USP, and sodium propionate, NF.

Promethazine hydrochloride is a racemic compound; the molecular formula is C17H20N2S•HCl and its molecular weight is 320.89.

Promethazine hydrochloride, a phenothiazine derivative, is chemically designated as 10-[2-(Dimethylamino)propyl] phenothiazine monohydrochloride. Its structural formula is:

Promethazine hydrochloride occurs as a white to faint yellow, practically odorless, crystalline powder which slowly oxidizes and turns blue on prolonged exposure to air. It is freely soluble in water and soluble in alcohol.

CLINICAL PHARMACOLOGY

Promethazine is a phenothiazine derivative which differs structurally from the antipsychotic phenothiazines by the presence of a branched side chain and no ring substitution. It is thought that this configuration is responsible for its relative lack (1/10 that of chlorpromazine) of dopaminergic Central Nervous System (CNS) action.

Promethazine is an H1 receptor blocking agent. In addition to its antihistaminic action, it provides clinically useful sedative and antiemetic effects. In therapeutic dosage, promethazine produces no significant effects on the cardiovascular system.

Promethazine is well absorbed from the gastrointestinal tract. Clinical effects are apparent within 20 minutes after oral administration and generally last four to six hours, although they may persist as long as 12 hours. Promethazine is metabolized by the liver to a variety of compounds; the sulfoxides of promethazine and N-demethylpromethazine are the predominant metabolites appearing in the urine.

INDICATIONS AND USAGE

Promethazine is useful for:

Perennial and seasonal allergic rhinitis.

Vasomotor rhinitis.

Allergic conjunctivitis due to inhalant allergens and foods.

Mild, uncomplicated allergic skin manifestations of urticaria and angioedema.

Amelioration of allergic reactions to blood or plasma.

Dermographism.

Anaphylactic reactions, as adjunctive therapy to epinephrine and other standard measures, after the acute manifestations have been controlled.

Preoperative, postoperative, or obstetric sedation.

Prevention and control of nausea and vomiting associated with certain types of anesthesia and surgery.

Therapy adjunctive to meperidine or other analgesics for control of postoperative pain.

Sedation in both children and adults, as well as relief of apprehension and production of light sleep from which the patient can be easily aroused.

Active and prophylactic treatment of motion sickness.

Antiemetic therapy in postoperative patients.

CONTRAINDICATIONS

Promethazine products are contraindicated for use in pediatric patients less than two years of age.

Promethazine is contraindicated in individuals known to be hypersensitive or to have had an idiosyncratic reaction to promethazine or to other phenothiazines.

Antihistamines are contraindicated for use in the treatment of lower respiratory tract symptoms, including asthma.

WARNINGS

BOXED WARNING

PROMETHAZINE SHOULD NOT BE USED IN PEDIATRIC PATIENTS LESS THAN 2 YEARS OF AGE BECAUSE OF THE POTENTIAL FOR FATAL RESPIRATORY DEPRESSION.

POSTMARKETING CASES OF RESPIRATORY DEPRESSION, INCLUDING FATALITIES, HAVE BEEN REPORTED WITH USE OF PROMETHAZINE IN PEDIATRIC PATIENTS LESS THAN 2 YEARS OF AGE. A WIDE RANGE OF WEIGHT-BASED DOSES OF PROMETHAZINE HAVE RESULTED IN RESPIRATORY DEPRESSION IN THESE PATIENTS.

CAUTION SHOULD BE EXERCISED WHEN ADMINISTERING PROMETHAZINE TO PEDIATRIC PATIENTS 2 YEARS OF AGE AND OLDER. IT IS RECOMMENDED THAT THE LOWEST EFFECTIVE DOSE OF PROMETHAZINE BE USED IN PEDIATRIC PATIENTS 2 YEARS OF AGE AND OLDER AND CONCOMITANT ADMINISTRATION OF OTHER DRUGS WITH RESPIRATORY DEPRESSANT EFFECTS BE AVOIDED.

Promethazine may cause marked drowsiness. Ambulatory patients should be cautioned against such activities as driving or operating dangerous machinery until it is known that they do not become drowsy or dizzy from promethazine therapy.

The sedative action of promethazine hydrochloride is additive to the sedative effects of CNS depressants; therefore, agents such as alcohol, narcotic analgesics, sedatives, hypnotics and tranquilizers should either be eliminated or given in reduced dosage in the presence of promethazine hydrochloride. When given concomitantly with promethazine hydrochloride, the dose of barbiturates should be reduced by at least one-half, and the dose of analgesic depressants, such as morphine or meperidine, should be reduced by one-quarter to one-half.

Promethazine may lower seizure threshold. This should be taken into consideration when administering to persons with known seizure disorders, or when giving in combination with narcotics or local anesthetics which may also affect seizure threshold.

Sedative drugs or CNS depressants should be avoided in patients with a history of sleep apnea.

Antihistamines should be used with caution in patients with narrow-angle glaucoma, stenosing peptic ulcer, pyloroduodenal obstruction and urinary bladder obstruction due to symptomatic prostatic hypertrophy and narrowing of the bladder neck.

Administration of promethazine has been associated with reported cholestatic jaundice.

Use in Pediatric Patients

PROMETHAZINE PRODUCTS ARE CONTRAINDICATED FOR USE IN PEDIATRIC PATIENTS LESS THAN TWO YEARS OF AGE.

CAUTION SHOULD BE EXERCISED WHEN ADMINISTERING PROMETHAZINE PRODUCTS TO PEDIATRIC PATIENTS 2 YEARS OF AGE AND OLDER BECAUSE OF THE POTENTIAL FOR FATAL RESPIRATORY DEPRESSION. RESPIRATORY DEPRESSION AND APNEA, SOMETIMES ASSOCIATED WITH DEATH, ARE STRONGLY ASSOCIATED WITH PROMETHAZINE PRODUCTS AND ARE NOT DIRECTLY RELATED TO INDIVIDUALIZED WEIGHT-BASED DOSING, WHICH MIGHT OTHERWISE PERMIT SAFE ADMINISTRATION. CONCOMITANT ADMINISTRATION OF PROMETHAZINE PRODUCTS WITH OTHER RESPIRATORY DEPRESSANTS HAS AN ASSOCIATION WITH RESPIRATORY DEPRESSION, AND SOMETIMES DEATH, IN PEDIATRIC PATIENTS.

ANTIEMETICS ARE NOT RECOMMENDED FOR TREATMENT OF UNCOMPLICATED VOMITING IN PEDIATRIC PATIENTS, AND THEIR USE SHOULD BE LIMITED TO PROLONGED VOMITING OF KNOWN ETIOLOGY. THE EXTRAPYRAMIDAL SYMPTOMS WHICH CAN OCCUR SECONDARY TO PROMETHAZINE PRODUCTS ADMINISTRATION MAY BE CONFUSED WITH THE CNS SIGNS OF UNDIAGNOSED PRIMARY DISEASE, e.g., ENCEPHALOPATHY OR REYE'S SYNDROME. THE USE OF PROMETHAZINE PRODUCTS SHOULD BE AVOIDED IN PEDIATRIC PATIENTS WHOSE SIGNS AND SYMPTOMS MAY SUGGEST REYE'S SYNDROME OR OTHER HEPATIC DISEASES.

Excessively large dosages of antihistamines, including Promethazine products, in pediatric patients may cause sudden death (see OVERDOSAGE). Hallucinations and convulsions have occurred with therapeutic doses and overdoses of Promethazine in pediatric patients. In pediatric patients who are acutely ill associated with dehydration, there is an increased susceptibility to dystonias with the use of promethazine HCl.

PRECAUTIONS

General

Promethazine should be used cautiously in persons with cardiovascular disease or with impairment of liver function.

Information for Patients

Promethazine may cause marked drowsiness or may impair the mental and/or physical abilities required for the performance of potentially hazardous tasks, such as driving a vehicle or operating machinery. Ambulatory patients should be told to avoid engaging in such activities until it is known that they do not become drowsy or dizzy from promethazine therapy. Children should be supervised to avoid potential harm in bike riding or in other hazardous activities.

The concomitant use of alcohol or other CNS depressants, including narcotic analgesics, sedatives, hypnotics and tranquilizers, may have an additive effect and should be avoided or their dosage reduced.

Patients should be advised to report any involuntary muscle movements or unusual sensitivity to sunlight.

Drug Interactions

The sedative action of promethazine is additive to the sedative effects of other CNS depressants, including alcohol, narcotic analgesics, sedatives, hypnotics, tricyclic antidepressants and tranquilizers; therefore, these agents should be avoided or administered in reduced dosage to patients receiving promethazine.

Drug/Laboratory Test Interactions

The following laboratory tests may be affected in patients who are receiving therapy with promethazine hydrochloride:

Pregnancy Tests

Diagnostic pregnancy tests based on immunological reactions between HCG and anti-HCG may result in false-negative or false-positive interpretations.

Glucose Tolerance Test

An increase in blood glucose has been reported in patients receiving promethazine.

Carcinogenesis, Mutagenesis, Impairment of Fertility

Long-term animal studies have not been performed to assess the carcinogenic potential of promethazine, nor are there other animal or human data concerning the carcinogenicity, mutagenicity or impairment of fertility with this drug. Promethazine was nonmutagenic in the Salmonella test system of Ames.

Pregnancy

Teratogenic Effects—Pregnancy Category C

Teratogenic effects have not been demonstrated in rat-feeding studies at doses of 6.25 and 12.5 mg/kg of promethazine. These doses are from approximately 2.1 to 4.2 times the maximum recommended total daily dose of promethazine for a 50-kg subject, depending upon the indication for which the drug is prescribed. Specific studies to test the action of the drug on parturition, lactation and development of the animal neonate were not done, but a general preliminary study in rats indicated no effect on these parameters. Although antihistamines, including promethazine, have been found to produce fetal mortality in rodents, the pharmacological effects of histamine in the rodent do not parallel those in man. There are no adequate and well-controlled studies of promethazine in pregnant women. Promethazine should be used during pregnancy only if the potential benefit justifies the potential risk to the fetus.

Nonteratogenic Effects

Promethazine taken within two weeks of delivery may inhibit platelet aggregation in the newborn.

Labor and Delivery

Promethazine, in appropriate dosage form, may be used alone or as an adjunct to narcotic analgesics during labor and delivery (See "INDICATIONS AND USAGE" and "DOSAGE AND ADMINISTRATION").

See also "Nonteratogenic Effects".

Nursing Mothers

It is not known whether promethazine is excreted in human milk. Caution should be exercised when promethazine is administered to a nursing woman.

Pediatric Use

PROMETHAZINE PRODUCTS ARE CONTRAINDICATED FOR USE IN PEDIATRIC PATIENTS LESS THAN TWO YEARS OF AGE (see WARNINGS-Black Box Warning and Use in Pediatric Patients).

Promethazine products should be used with caution in pediatric patients 2 years of age and older (see WARNINGS-Use in Pediatric Patients).

Geriatric Use

Clinical studies of Promethazine formulations did not include sufficient numbers of subjects aged 65 and over to determine whether they respond differently from younger subjects. Other reported clinical experience has not identified differences in responses between the elderly and younger patients. In general, dose selection for an elderly patient should be cautious, usually starting at the low end of the dosing range, reflecting the greater frequency of decreased hepatic, renal or cardiac function, and of concomitant disease or other drug therapy.

Sedating drugs may cause confusion and over-sedation in the elderly; elderly patients generally should be started on low doses of Promethazine products and observed closely.

ADVERSE REACTIONS

CNS–Sedation, sleepiness, occasional blurred vision, dryness of mouth, dizziness; rarely confusion, disorientation and extrapyramidal symptoms such as oculogyric crisis, torticollis and tongue protrusion (usually in association with parenteral injection or excessive dosage).

Cardiovascular–Increased or decreased blood pressure.

Dermatologic–Rash, rarely photosensitivity.

Hematologic–Rarely leukopenia, thrombocytopenia; agranulocytosis (1 case).

Gastrointestinal–Nausea and vomiting.

OVERDOSAGE

Signs and symptoms of overdosage with promethazine range from mild depression of the CNS and cardiovascular system to profound hypotension, respiratory depression and unconsciousness.

Stimulation may be evident, especially in children and geriatric patients. Convulsions may rarely occur. A paradoxical reaction has been reported in children receiving single doses of 75 mg to 125 mg orally, characterized by hyperexcitability and nightmares.

Atropine-like signs and symptoms – dry mouth, fixed dilated pupils, flushing, as well as gastrointestinal symptoms, may occur.

Treatment

The treatment of overdosage with promethazine is essentially symptomatic and supportive. Only in cases of extreme overdosage or individual sensitivity do vital signs including respiration, pulse, blood pressure, temperature and EKG need to be monitored. Activated charcoal orally or by lavage may be given, or sodium or magnesium sulfate orally as a cathartic. Attention should be given to the reestablishment of adequate respiratory exchange through provision of a patent airway and institution of assisted or controlled ventilation. Diazepam may be used to control convulsions. Acidosis and electrolyte losses should be corrected. Note that any of the depressant effects of promethazine are not reversed by naloxone. Avoid analeptics which may cause convulsions.

Severe hypotension usually responds to the administration of norepinephrine or phenylephrine. EPINEPHRINE SHOULD NOT BE USED since its use in patients with partial adrenergic blockade may further lower the blood pressure.

Limited experience with dialysis indicates that it is not helpful.

DOSAGE AND ADMINISTRATION

Promethazine products are contraindicated for children under 2 years of age (see WARNINGS-Black Box Warning and Use in Pediatric Patients).

ALLERGY

The average oral dose is 25 mg taken before retiring; however, 12.5 mg may be taken before meals and on retiring, if necessary. Children tolerate this product well. Single 25 mg doses at bedtime or 6.25 to 12.5 mg taken three times daily will usually suffice. After initiation of treatment in children or adults, dosage should be adjusted to the smallest amount adequate to relieve symptoms.

Promethazine hydrochloride rectal suppositories may be used if the oral route is not feasible, but oral therapy should be resumed as soon as possible if continued therapy is indicated.

The administration of promethazine hydrochloride in 25 mg doses will control minor transfusion reactions of an allergic nature.

MOTION SICKNESS

The average adult dose is 25 mg taken twice daily. The initial dose should be taken one-half to one hour before anticipated travel and be repeated 8 to 12 hours later, if necessary. On succeeding days of travel, it is recommended that 25 mg be given on arising and again before the evening meal. For children, promethazine tablets, syrup or rectal suppositories, 12.5 to 25 mg, twice daily, may be administered.

NAUSEA AND VOMITING

The average effective dose of promethazine for the active therapy of nausea and vomiting in children or adults is 25 mg. When oral medication cannot be tolerated, the dose should be given parenterally (cf. promethazine hydrochloride injection) or by rectal suppository. 12.5 to 25 mg doses may be repeated as necessary at 4- to 6-hour intervals.

For nausea and vomiting in children, the usual dose is 0.5 mg per pound of body weight, and the dose should be adjusted to the age and weight of the patient and the severity of the condition being treated.

For prophylaxis of nausea and vomiting, as during surgery and the postoperative period, the average dose is 25 mg repeated at 4- to 6-hour intervals, as necessary.

SEDATION

This product relieves apprehension and induces a quiet sleep from which the patient can be easily aroused. Administration of 12.5 to 25 mg promethazine by the oral route or by rectal suppository at bedtime will provide sedation in children. Adults usually require 25 to 50 mg for nighttime, presurgical, or obstetrical sedation.

PRE- AND POSTOPERATIVE USE

Promethazine in 12.5 to 25 mg doses for children and 50 mg doses for adults the night before surgery relieves apprehension and produces a quiet sleep.

For preoperative medication, children require doses of 0.5 mg per pound of body weight in combination with an equal dose of meperidine and the appropriate dose of an atropine-like drug.

Usual adult dosage is 50 mg promethazine with an equal amount of meperidine and the required amount of a belladonna alkaloid.

Postoperative sedation and adjunctive use with analgesics may be obtained by the administration of 12.5 to 25 mg in children and 25 to 50 mg doses in adults.

Promethazine Syrup Plain is contraindicated for children under 2 years of age.

HOW SUPPLIED

Promethazine Hydrochloride Syrup, USP 6.25 mg/5 mL NDC 21695-703-04 is supplied as a clear, green syrup. Available in 4 fl oz (118 mL) Bottles.

RECOMMENDED STORAGE

Store at 20 ° to 25 °C (68 ° to 77 °F). [See USP Controlled Room Temperature].

KEEP TIGHTLY CLOSED

PROTECT FROM LIGHT

Dispense in a tight, light-resistant container as defined in the USP.

Rx Only

Product No.: 7608

Manufactured By:
Morton Grove Pharmaceuticals, Inc.
Morton Grove, IL 60053

A50-7608-04

REV. 07-05

Repackaged by:

Rebel Distributors Corp

Thousand Oaks, C

a 91320